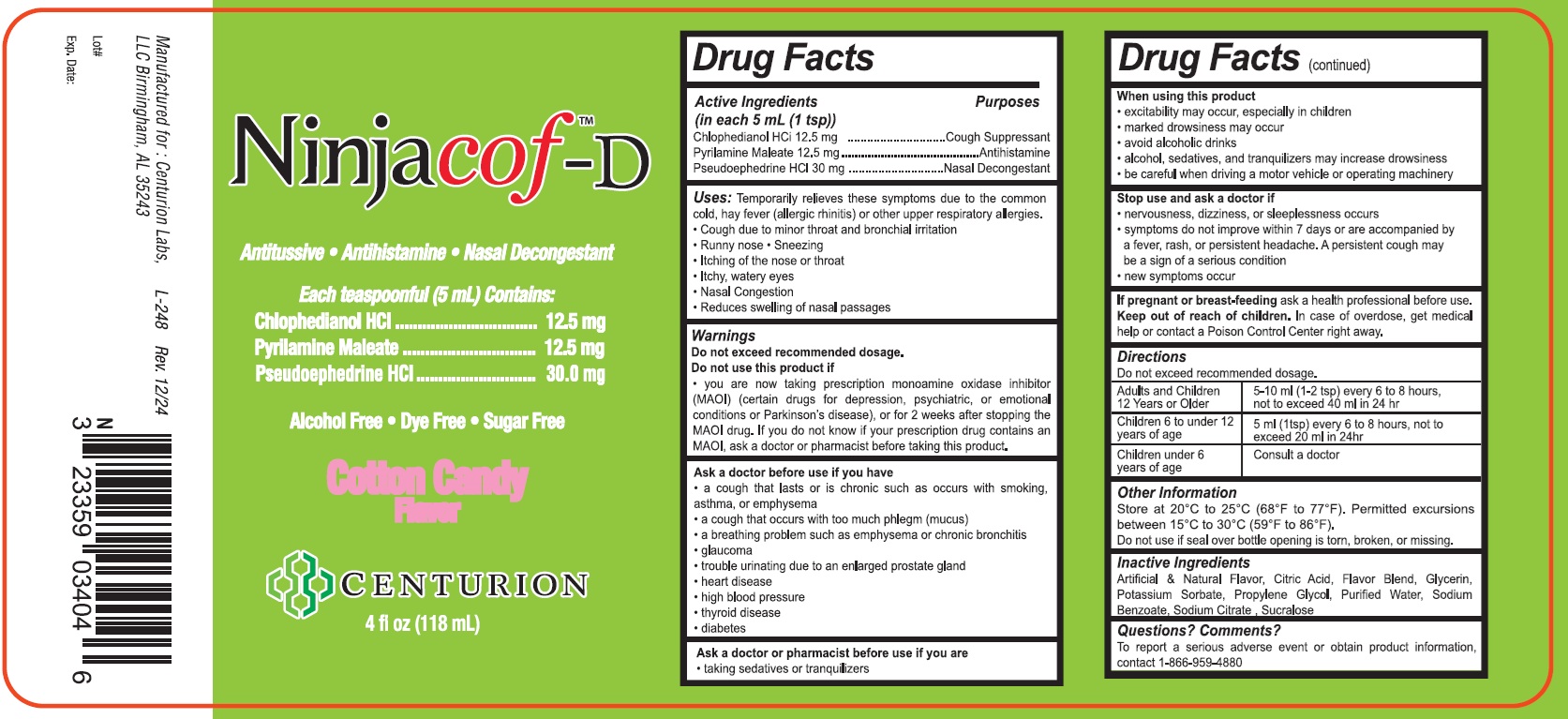 DRUG LABEL: Ninjacof-D
NDC: 23359-034 | Form: LIQUID
Manufacturer: Centurion Labs, LLC
Category: otc | Type: HUMAN OTC DRUG LABEL
Date: 20251231

ACTIVE INGREDIENTS: CHLOPHEDIANOL HYDROCHLORIDE 12.5 mg/5 mL; PYRILAMINE MALEATE 12.5 mg/5 mL; PSEUDOEPHEDRINE HYDROCHLORIDE 30 mg/5 mL
INACTIVE INGREDIENTS: CITRIC ACID ACETATE; GLYCERIN; PROPYLENE GLYCOL; SODIUM BENZOATE; SODIUM CITRATE; SUCRALOSE; WATER

Ninjacof D

Drug Facts

Active Ingredients (in each 5 mL (1 tsp)) Purpose

Chlophedianol HCl 12.5 mg...........................Cough Suppressant

Pyrilamine Maleate 12.5 mg...........................Antihistamine

Pseudoephedrine HCl 30 mg...........................Nasal Decongestant

Purpose

Antitussive

Antihistamine

Nasal Decongestant

Uses:

Temporarily relieves these symptoms due to the common cold, hay fever (allergic rhinitis) or other upper respiratory allergies.

- Cough due to minor throat and bronchial irritation
- Runny Nose
- Sneezing
- Itching of the nose or throat
- Itchy, watery eyes
- Nasal Congestion
- Reduces swelling of nasal passages

WARNINGS

Do not exceed recommended dosage

Do not use this product if

- you are now taking prescription monoamine oxidase inhibitor (MAOI) (certain drugs for depression, psychiatric, or emotional conditions or Parkinson's disease), or for 2 weeks after stopping the MAOI drug. If you do not know if your prescription drug contains an MAOI, ask a doctor or pharmacist before taking this product.

Ask a doctor before use if you have

- a cough that lasts or is chronic such as occurs with smoking, asthma, or emphysema
- a cough that occurs with too much phlegm (mucus)
- a breathing problem such as emphysema or chronic bronchitis
- glaucoma
- trouble urinating due to an enlarged prostate gland
- heart disease
- high blood pressure
- thyroid disease
- diabetes

Ask doctor or pharmacist before use if you are

- taking sedatives or tranquilizers

When using this product

- excitability may occur, especially in children
- marked drowsiness may occur
- avoid alcoholic beverages
- alcohol, sedatives, and tranquilizers may increase drowsiness
- be careful when driving a motor vehicle or operating machinery

Stop use and ask a doctor if

- nervousness, dizziness, or sleeplessness occurs
- symptoms do not improve within 7 days or are accompanied by a fever,
- rash, or persistent headache. A persistent cough may be a sign of a serious condition
- new symptoms occur

If Pregnant or breast feeding

Ask a health professional before use.

Keep out of reach of children

In case of overdose, get medical help or contact a Poison Control Center right away.

Directions

Do not exceed recommended dosage.

Adults and Children 12 Years or Older. | 5-10ml (1-2 tsp) every 6 to 8 hours not to exceed 40ml in 24hr
Children 6-12 | 5ml (1 tsp) every 6 to 8 hours not to exceed 20ml in 24hr
Children under 6 years of age | Consult a doctor.

Other Information

Store at 59° - 85° F (15° - 30° C)

Inactive Ingredients

Citric Acid, Glycerin, Natural & Artificial Flavors, Propylene Glycol, Sodium Benzoate, Sodium Citrate, Sucralose, Water

Questions? Comments?

To report a serious adverse event or obtain product information, contact 1-866-959-4880